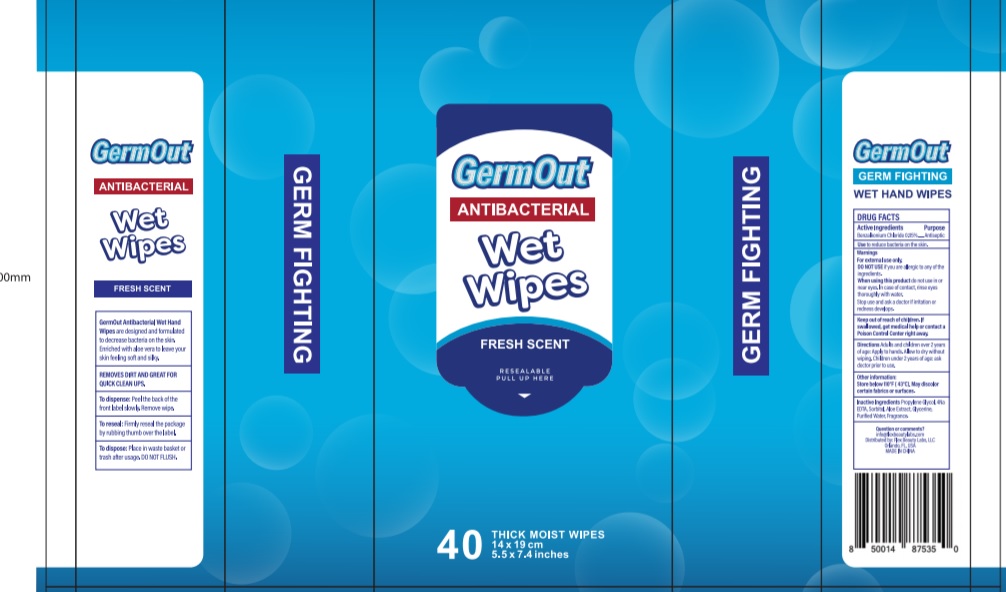 DRUG LABEL: ANTIBACTERIAL WET WIPES
NDC: 70031-400 | Form: CLOTH
Manufacturer: Tianjin Yansheng Industrial Trade Company
Category: otc | Type: HUMAN OTC DRUG LABEL
Date: 20200406

ACTIVE INGREDIENTS: BENZALKONIUM CHLORIDE 0.115 g/1 1
INACTIVE INGREDIENTS: PROPYLENE GLYCOL; EDETIC ACID; SORBITOL; ALOE; WATER; GLYCERIN

GERM OUT Antibacterial 40 Count Wet Wipes

Active Ingredient

Benzalkonium chloride 0.115%

Purpose: Antibacterial

Uses

For hand washing to decrease bacterial on the skin. May be used on face arms and legs.

Warnings

For external use only

Keep out of eyes. In case of eye contact, rinse with water.

If irritation develops discontinue use. Consult a doctor if irritation persists more than 72 hours

If swallowed, seek medical attention or contact a Poison Control Center.

KEEP OUT OF REACH OF CHILDREN

Keep out of the reach of children, except with adult supervision.

DOSAGE AND ADMINISTRATION

Direction for dispensing:

Remove lid from canister.

Lift flap in center of lid.

Pull up corner of center sheet, twist to a point and thread through dispenser hole in lid.

Do not push finger through opening.

Replace lid and pull sheet out at an angle. The next sheet pops up automatically.

when finished reseal by closing lid flap to retain moisture.

Direction for use:

Thoroughly wipe hands and face as desired.

Allow to dry without wiping.

Discard wipe in trash receptacle after use. Do not flush.

Inactive Ingredients

Propylene glycol, 4Na EDTA, Sorbitol, Aloe Extract, Purified Water, Fragrance, Glycerine.